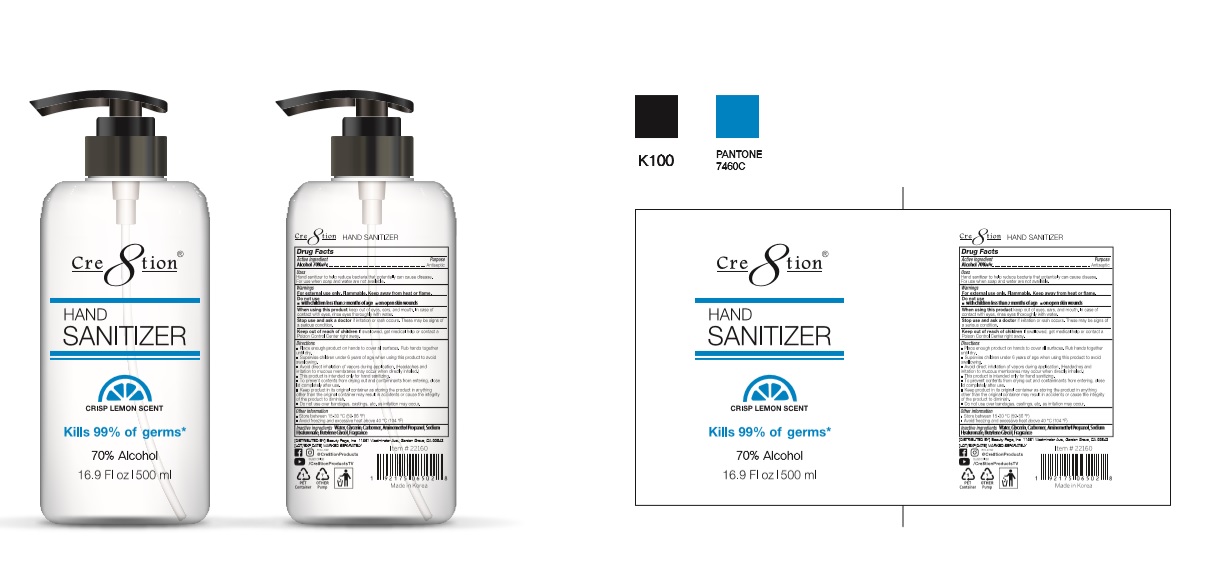 DRUG LABEL: Cre8tion HAND SANITIZER
NDC: 74339-2257 | Form: GEL
Manufacturer: PL COSMETIC
Category: otc | Type: HUMAN OTC DRUG LABEL
Date: 20200412

ACTIVE INGREDIENTS: ALCOHOL 350 mL/500 mL
INACTIVE INGREDIENTS: GLYCERIN; CARBOMER HOMOPOLYMER, UNSPECIFIED TYPE; WATER; BUTYLENE GLYCOL; HYALURONATE SODIUM; AMINOMETHYLPROPANOL

Cre8tion HAND SANITIZER 500 ml : 74339-2257